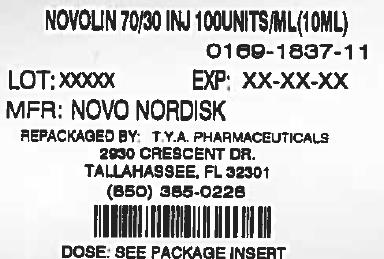 DRUG LABEL: Novolin
                                    
NDC: 64725-1837 | Form: INJECTION, SUSPENSION
Manufacturer: TYA Pharmaceuticals
Category: otc | Type: HUMAN OTC DRUG LABEL
Date: 20130830

ACTIVE INGREDIENTS: INSULIN HUMAN 100 [USP'U]/1 mL
INACTIVE INGREDIENTS: GLYCERIN; METACRESOL; PHENOL; PROTAMINE SULFATE; SODIUM PHOSPHATE, DIBASIC, DIHYDRATE; ZINC CHLORIDE; HYDROCHLORIC ACID; SODIUM HYDROXIDE; WATER

Novolin 70/30, 70% NPH, Human Insulin Isophane Suspension and 30% Regular, Human Insulin Injection (recombinant DNA origin)®

PATIENT PACKAGE INSERT

Patient Information for Novolin 70/30®

NOVOLIN 70/30 (NO-voe-lin)®

70% NPH, Human Insulin Isophane Suspension and

30% Regular, Human Insulin Injection

(recombinant DNA origin) units/mL 100

PURPOSE

Important:

Do not change the type of insulin you use unless told to do so by your healthcare provider. The amount of insulin you take as well as the best time for you to take your insulin may need to change if you take a different type of insulin. Know your insulin.

Make sure that you know the type and strength of insulin that is prescribed for you.

Read the Patient Information leaflet that comes with Novolin 70/30 before you start taking it and each time you get a refill. There may be new information. This leaflet does not take the place of talking with your healthcare provider about your diabetes or your treatment. Make sure you know how to manage your diabetes. Ask your healthcare provider if you have any questions about managing your diabetes.®

What is Novolin 70/30?®

Novolin 70/30 is a man-made insulin (recombinant DNA origin) which is a mixture of 70% NPH, Human Insulin Isophane Suspension and 30% Regular, Human Insulin Injection that is structurally identical to the insulin produced by the human pancreas that is used to control high blood sugar in patients with diabetes mellitus.®

DO NOT USE

Who should not use Novolin 70/30?®

Do not take Novolin 70/30 if:®

- Your blood sugar is too low (hypoglycemia).
- You are allergic to anything in Novolin 70/30. See the end of this leaflet for a complete list of ingredients in Novolin 70/30. Check with your healthcare provider if you are not sure. ®®

ASK YOUR DOCTOR

Tell your healthcare provider:

- Medical conditions can affect your insulin needs and your dose of Novolin 70/30. about all of your medical conditions.®
- You and your healthcare provider should talk about the best way to manage your diabetes while you are pregnant or breastfeeding. Novolin 70/30 has not been studied in pregnant or nursing women. if you are pregnant or breastfeeding.®
- including prescription and non-prescription medicines, vitamins and herbal supplements. Many medicines can affect your blood sugar levels and your insulin needs. Your Novolin 70/30 dose may need to change if you take other medicines. about all of the medicines you take,®
- if you take any other medicines, especially ones commonly called TZDs (thiazolidinediones).
- If you have heart failure, it may get worse while you take TZDs with Novolin 70/30. if you have heart failure or other heart problems.®

Keep a list of your medicines with you to show all your healthcare providers when you get a new medicine. Know the medicines you take.

DOSAGE AND ADMINISTRATION

How should I take Novolin 70/30?®

Only use Novolin 70/30 if it appears cloudy or milky. There may be air bubbles. This is normal. If the precipitate (the white deposit at the bottom of the vial) has become lumpy or granular in appearance or has formed a deposit of solid particles on the wall of the vial, do not use it, and call Novo Nordisk at 1-800-727-6500. This insulin should not be used if the liquid in the vial remains clear after the vial has been gently rotated.®

Novolin 70/30 comes in:®

- 10 mL vials (small bottles) for use with syringe

INDICATIONS AND USAGE

Talk to your healthcare provider if you have any questions. Your healthcare provider should show you how to inject Novolin 70/30 before you start taking it. Follow your healthcare provider’s instructions to make changes to your insulin dose. Read the instructions for use that come with your Novolin 70/30 product.®®

- Take Novolin 70/30 exactly as prescribed.®
- The effects of Novolin 70/30 start working ½ hour after injection. Novolin 70/30 is an intermediate-acting insulin.®®
- The greatest blood sugar lowering effect is between 2 and 12 hours after the injection. This blood sugar lowering may last up to 24 hours.
- , any change of insulin should be made cautiously and only under medical supervision. Doses of oral anti-diabetic medicines may also need to change, if your insulin is changed. While using Novolin 70/30®
- with any insulins. Do not mix Novolin 70/30®
- Novolin 70/30 may affect your blood sugar levels sooner if you inject it into the skin of your stomach area. Inject Novolin 70/30 into the skin of your stomach area, upper arms, buttocks or upper legs.®® Never inject Novolin 70/30 into a vein or into a muscle.®
- Change (rotate) your injection site within the chosen area (for example, stomach or upper arm) with each dose. Do not inject into the same spot for each injection.
- You can treat mild low blood sugar (hypoglycemia) by drinking or eating something sugary right away (fruit juice, sugar candies, or glucose tablets). It is important to treat low blood sugar (hypoglycemia) right away because it could get worse and you could pass out (become unconscious). If you pass out, you will need help from another person or emergency medical services right away, and will need treatment with a glucagon injection or treatment at a hospital. See “What are the possible side effects of Novolin 70/30?” for more information on low blood sugar (hypoglycemia). If you take too much Novolin 70/30, your blood sugar may fall low (hypoglycemia).®®
- If high blood sugar (hyperglycemia) is not treated it can lead to diabetic ketoacidosis, which can lead to serious problems, like loss of consciousness (passing out), coma or even death. Follow your healthcare provider’s instructions for treating high blood sugar (hyperglycemia), and talk to your healthcare provider if high blood sugar is a problem for you. Severe or continuing high blood sugar (hyperglycemia) requires prompt evaluation and treatment by your healthcare provider. Know your symptoms of high blood sugar (hyperglycemia) and diabetic ketoacidosis which may include: If you forget to take your dose of Novolin 70/30, your blood sugar may go too high (hyperglycemia).®

  ∘ increased thirst
  ∘ frequent urination and dehydration
  ∘ confusion or drowsiness
  ∘ loss of appetite

  ∘ fruity smell on breath
  ∘ high amounts of sugar and ketones in your urine
  ∘ nausea, vomiting (throwing up) or stomach pain
  ∘ a hard time breathing

Ask your healthcare provider how often you should check your blood sugar levels for hypoglycemia (too low blood sugar) and hyperglycemia (too high blood sugar). Check your blood sugar levels.

Your insulin dosage may need to change because of:

- illness
- stress
- other medicines you take

- change in diet
- change in physical activity or exercise
- surgery

See the end of this patient information for instructions about preparing and giving the injection.

What should I avoid while using Novolin 70/30?®

- Alcohol, including beer and wine, may affect your blood sugar when you take Novolin 70/30. Alcohol.®
- . You may have difficulty concentrating or reacting if you have low blood sugar (hypoglycemia). Be careful when you drive a car or operate machinery. Ask your healthcare provider if it is alright to drive if you often have: Driving and operating machinery
  ∘ low blood sugar
  ∘ decreased or no warning signs of low blood sugar

ADVERSE EFFECTS

What are the possible side effects of Novolin 70/30?®

- Symptoms of hypoglycemia (low blood sugar) may include: Low blood sugar (hypoglycemia).

- sweating
- dizziness or lightheadedness
- shakiness
- hunger
- fast heart beat
- tingling of lips and tongue

- trouble concentrating or confusion
- blurred vision
- slurred speech
- anxiety, irritability or mood changes
- headache

Severe low blood sugar (hypoglycemia) can cause unconsciousness (passing out), seizures, and death. Know your symptoms of low blood sugar. Follow your healthcare provider’s instructions for treating low blood sugar. Talk to your healthcare provider if low blood sugar is a problem for you.

- a rash over your whole body, have trouble breathing, a fast heartbeat, or sweating. Serious allergic reaction (whole body reaction). Get medical help right away if you develop
- You may get redness, swelling, and itching at the injection site. If you keep having skin reactions, or they are serious, talk to your healthcare provider. You may need to stop using Novolin 70/30 and use a different insulin. Do not inject insulin into skin that is red, swollen, or itchy. Reactions at the injection site (local allergic reaction).®
- Change (rotate) where you inject your insulin to help prevent these skin changes from happening. Do not inject insulin into this type of skin. Skin thickens or pits at the injection site (lipodystrophy).
- Swelling of your hands and feet
- Taking certain diabetes pills called thiazolidinediones or “TZDs” with Novolin 70/30 may cause heart failure in some people. This can happen even if you have never had heart failure or heart problems before. If you already have heart failure it may get worse while you take TZDs with Novolin 70/30. Your healthcare provider should monitor you closely while you are taking TZDs with Novolin 70/30. Tell your healthcare provider if you have any new or worse symptoms of heart failure including: Heart Failure.®®®
  ∘ shortness of breath
  ∘ swelling of your ankles or feet
  ∘ sudden weight gain

Treatment with TZDs and Novolin 70/30 may need to be adjusted or stopped by your healthcare provider if you have new or worse heart failure.®

- Vision changes
- Low potassium in your blood (hypokalemia)

These are not all of the possible side effects from Novolin 70/30. Ask your healthcare provider or pharmacist for more information.®

Call your doctor for medical advice about side effects. You may report side effects to FDA at 1-800-FDA-1088.

STORAGE AND HANDLING

How should I store Novolin 70/30?®

All Unopened Novolin 70/30:®

- Keep all unopened Novolin 70/30 in the refrigerator between 36° to 46°F (2° to 8°C).®
- Do not freeze. Do not use Novolin 70/30 if it has been frozen. ®
- If refrigeration is not possible, the unopened vial may be kept at room temperature for up to 6 weeks (42 days), as long as it is kept at or below 77°F (25°C).
- Keep unopened Novolin 70/30 in the carton to protect from light. ®

Novolin 70/30 in use:®

Vials

- Keep at room temperature below 77°F (25°C) for up to 6 weeks (42 days).
- Keep vials away from direct heat or light.
- Throw away an opened vial after 6 weeks (42 days) of use, even if there is insulin left in the vial.
- Unopened vials can be used until the expiration date on the Novolin 70/30 label, if the medicine has been stored in a refrigerator. ®

General advice about Novolin 70/30®

Novolin 70/30 is used for the treatment of diabetes only. Medicines are sometimes prescribed for conditions that are not mentioned in the patient leaflet. Do not use Novolin 70/30 for a condition for which it was not prescribed. Do not give Novolin 70/30 to other people, even if they have the same symptoms you have. It may harm them.®®®

This leaflet summarizes the most important information about Novolin 70/30. If you would like more information about Novolin 70/30 or diabetes, talk with your healthcare provider. For more information, call 1-800-727-6500 or visit www.novonordisk-us.com.®®

Helpful information for people with diabetes is published by the American Diabetes Association, 1701 N Beauregard Street, Alexandria, VA 22311 and on www.diabetes.org.

ACTIVE INGREDIENTS

Novolin 70/30 ingredients include:®

- 70% NPH, Human Insulin Isophane Suspension and 30% Regular, Human Insulin Injection (recombinant DNA origin)

INACTIVE INGREDIENTS

Novolin 70/30 ingredients include:®

- Zinc chloride
- Sodium hydroxide
- Phenol
- Disodium phosphate dihydrate

- Metacresol
- Glycerol
- Hydrochloric acid
- Protamine sulfate
- Water for injections

All Novolin 70/30 vials are latex-free.®

Date of issue: March 9, 2013

Version: 6

Novolin and Novo Nordisk are registered trademarks of Novo Nordisk A/S.®®

© 2005-2013 Novo Nordisk

Manufactured by:

Novo Nordisk A/S

DK-2880 Bagsvaerd, Denmark

For information about Novolin 70/30 contact:®

Novo Nordisk Inc.

800 Scudders Mill Road

Plainsboro, New Jersey 08536

Patient Instructions for Use

Novolin 70/30 10 mL vial (100 Units/mL, U-100)®

Before starting, gather all of the supplies that you will need to use for preparing and giving your insulin injection.

Never re-use syringes and needles.

How should I use the Novolin 70/30 vial?

1. Check to make sure that you have the correct type of insulin.
2. Look at the vial and the insulin. The insulin should be a cloudy or milky suspension. The tamper-resistant cap should be in place before the first use. If the cap had been removed before your first use of the vial, or if the precipitate (the white deposit at the bottom of the vial) has become lumpy or granular in appearance or has formed a deposit of solid particles on the wall of the vial, do not use it, and call Novo Nordisk at 1-800-727-6500.
3. Wash your hands with soap and water. If you clean your injection site with an alcohol swab, let the injection site dry before you inject. Talk with your healthcare provider about how to rotate injection sites and how to give an injection.
4. If you are using a new vial, pull off the tamper-resistant cap. Wipe the rubber stopper with an alcohol swab.
5. Roll the vial gently 10 times in your hands to mix it. This procedure should be carried out with the vial in a horizontal position. The rolling procedure must be repeated until the suspension appears uniformly white and cloudy. Shaking right before the dose is drawn into the syringe may cause bubbles or froth, which could cause you to draw up the wrong dose of insulin.
6. Pull back the plunger on the syringe until the black tip reaches the marking for the number of units you will inject.
7. Push the needle through the rubber stopper of the vial, and push the plunger all the way in to force air into the vial.
8. Turn the vial and syringe upside down and slowly pull the plunger back to a few units beyond the correct dose.
9. If there are any air bubbles, tap the syringe gently with your finger to raise the air bubbles to the top. Then slowly push the plunger to the marking for your correct dose. This process should move any air bubbles present in the syringe back into the vial.
10. Check to make sure you have the right dose of Novolin 70/30 in the syringe.
11. Pull the syringe with needle out of the vial’s rubber stopper.
12. Your doctor should tell you if you need to pinch the skin before inserting the needle. This can vary from patient to patient so it is important to ask your doctor if you did not receive instructions on pinching the skin. Insert the needle into the skin. Press the plunger of the syringe to inject the insulin. When you are finished injecting the insulin, pull the needle out of your skin. You may see a drop of Novolin 70/30 at the needle tip. This is normal and has no effect on the dose you just received. If you see blood after you take the needle out of your skin, press the injection site lightly with a piece of gauze or an alcohol wipe. Do not rub the area.
13. After your injection, do not recap the needle. Place used syringes, needles and used insulin vials in a disposable puncture-resistant sharps container, or some type of hard plastic or metal container with a screw on cap such as a detergent bottle or coffee can.
14. Ask your healthcare provider about the right way to throw away used syringes and needles. There may be state or local laws about the right way to throw away used syringes and needles. Do not throw away used needles and syringes in household trash or recycle.